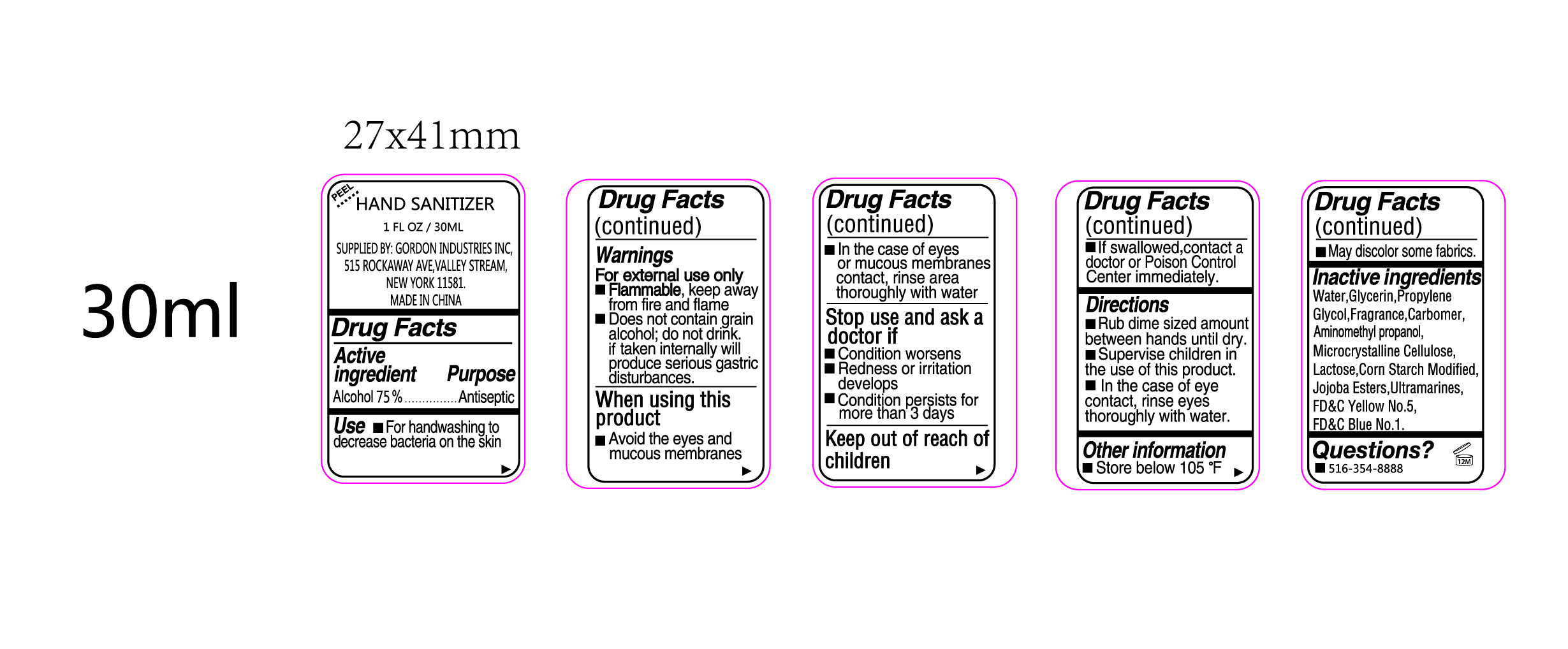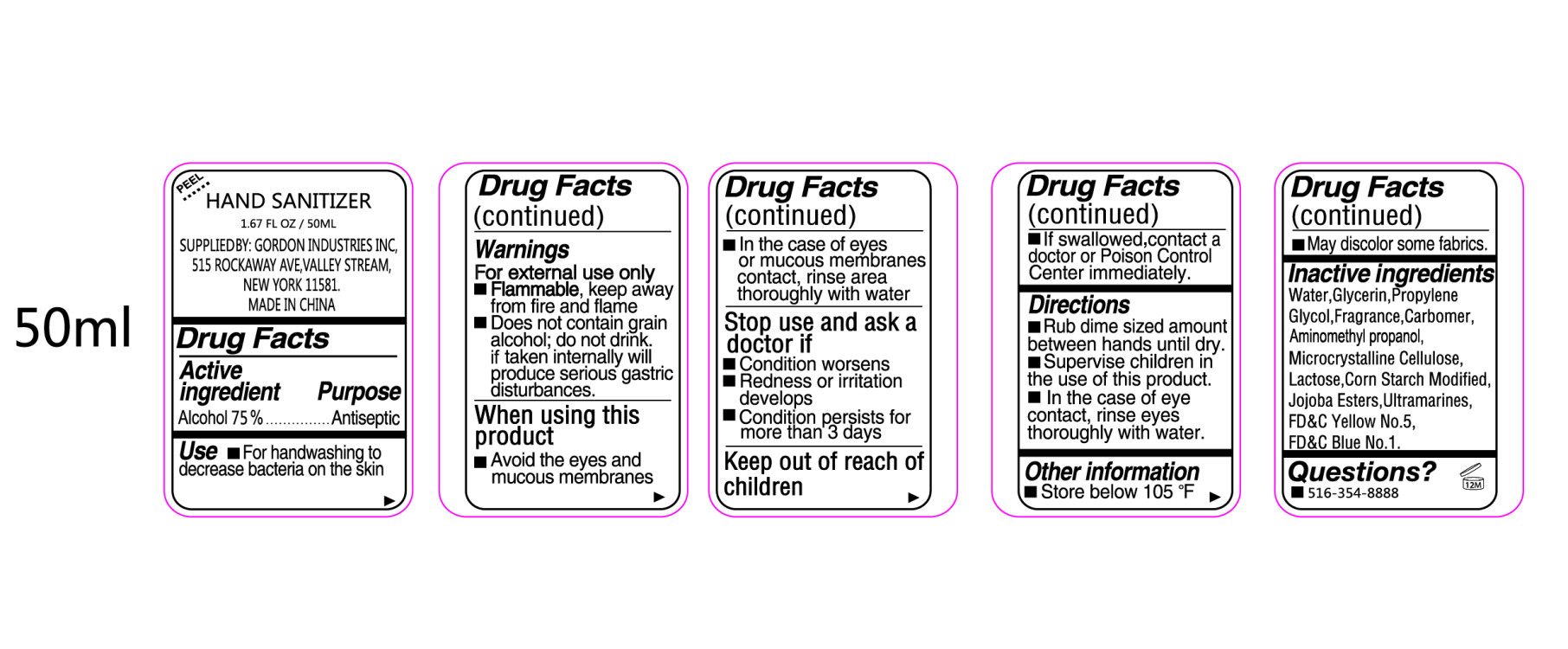 DRUG LABEL: Hand Sanitizer
NDC: 74979-001 | Form: LIQUID
Manufacturer: Robert Gordon Ind. Ltd.
Category: otc | Type: HUMAN OTC DRUG LABEL
Date: 20240209

ACTIVE INGREDIENTS: ALCOHOL 0.75 mL/1 mL
INACTIVE INGREDIENTS: WATER; GLYCERIN; PROPYLENE GLYCOL; CARBOMER HOMOPOLYMER, UNSPECIFIED TYPE; AMINOMETHYLPROPANOL; MICROCRYSTALLINE CELLULOSE; LACTOSE, UNSPECIFIED FORM; STARCH, CORN; FD&C YELLOW NO. 5; FD&C BLUE NO. 1

Hand Sanitizer

Active ingredient

Alcohol 75%

Purpose

Antiseptic

Use

- For hand washing to decrease bacteria on the skin

Warnings

For External Use Only.

- Flammable, keep away from fire and flame
- Does not contain grain alcohol; do not drink. If taken internally will produce serious gastric disturbances.

When using this product

- Avoid the eyes and mucous membranes
- In case of eyes or mucous membranes contact, rinse area thoroughly with water

Stop use and ask a doctor if

- Condition worsens
- Redness or irritation develops
- Condition persists for more than 3 days

Keep out of reach of children.

- If swallowed, contact a doctor or Poison Control Center immediately.

Directions

- Rub dime sized amount between hands until dry.
- Supervise children in the use of this product.
- In the case of eye contact, rinse eyes thoroughly with wtaer.

Other information

- Store below 105oF
- May discolor some fabrics.

Inactive Ingredients

Water, Glycerin, Propylene Glycol, Fragrance, Carbomer, Aminomethyl propanol, Microcrystalline Cellulose, Lactose, Corn Starch Modified, Jojoba Esters, Ultramarines, FD&C Yellow No. 5, FD&C Blue No. 1

Questions?

- 516-354-8888